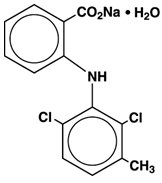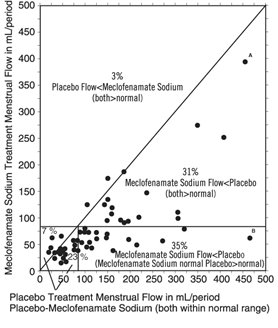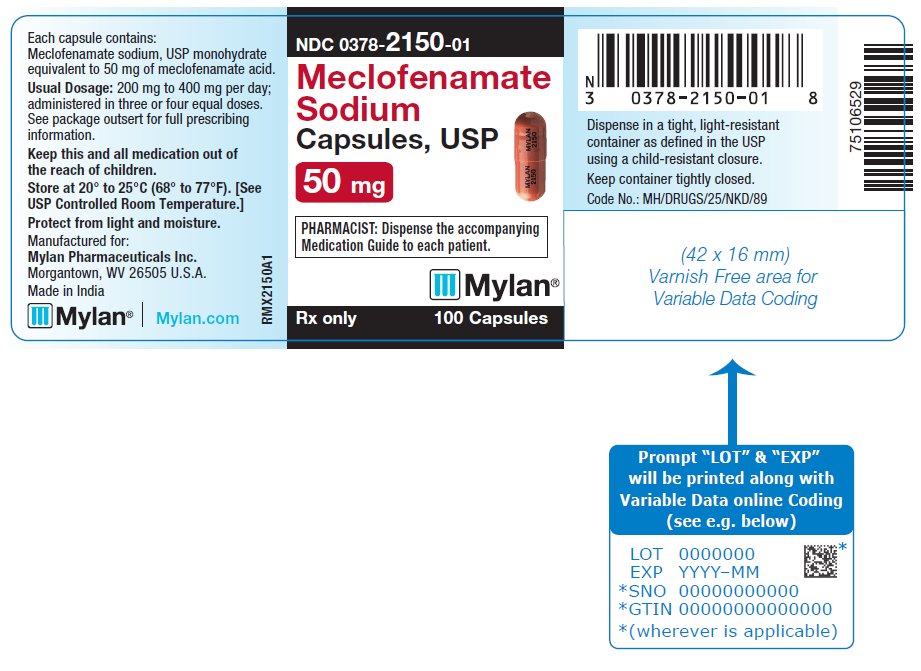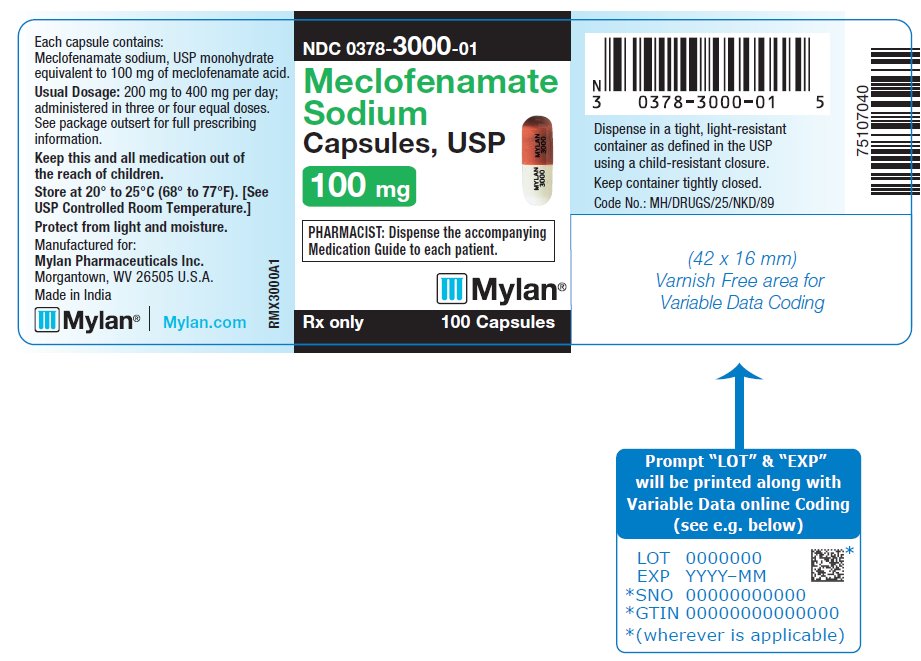 DRUG LABEL: Meclofenamate Sodium
NDC: 0378-2150 | Form: CAPSULE
Manufacturer: Mylan Pharmaceuticals Inc.
Category: prescription | Type: HUMAN PRESCRIPTION DRUG LABEL
Date: 20241211

ACTIVE INGREDIENTS: MECLOFENAMATE SODIUM 50 mg/1 1
INACTIVE INGREDIENTS: SILICON DIOXIDE; D&C YELLOW NO. 10; FD&C BLUE NO. 1; FD&C RED NO. 3; GELATIN, UNSPECIFIED; MAGNESIUM STEARATE; MICROCRYSTALLINE CELLULOSE; STARCH, CORN; SODIUM LAURYL SULFATE; TITANIUM DIOXIDE; FERROSOFERRIC OXIDE; FD&C BLUE NO. 2; FD&C RED NO. 40; PROPYLENE GLYCOL; SHELLAC

BOXED WARNING

Cardiovascular Thrombotic Events

- Nonsteroidal anti-inflammatory drugs (NSAIDs) cause an increased risk of serious cardiovascular thrombotic events, including myocardial infarction and stroke, which can be fatal. This risk may occur early in treatment and may increase with duration of use (see WARNINGS and PRECAUTIONS).
- Meclofenamate sodium capsules are contraindicated in the setting of coronary artery bypass graft (CABG) surgery (see CONTRAINDICATIONS and WARNINGS).

Gastrointestinal Risk

- NSAIDs cause an increased risk of serious gastrointestinal adverse events including bleeding, ulceration, and perforation of the stomach or intestines, which can be fatal. These events can occur at any time during use and without warning symptoms. Elderly patients are at greater risk for serious gastrointestinal events. (See WARNINGS).

DESCRIPTION

Meclofenamate sodium is N-(2,6-dichloro-m-tolyl) anthranilic acid, sodium salt, monohydrate. It is an anti-inflammatory drug for oral administration. Meclofenamate sodium capsules, USP contain 50 mg or 100 mg meclofenamic acid as the sodium salt and the following inactive ingredients: colloidal silicon dioxide, D&C Yellow No. 10, FD&C Blue No. 1, FD&C Red No. 3, gelatin, magnesium stearate, microcrystalline cellulose, pregelatinized starch (corn), sodium lauryl sulfate and titanium dioxide.

In addition, the imprinting ink contains black iron oxide, D&C Yellow No. 10 Aluminum Lake, FD&C Blue No. 1 Aluminum Lake, FD&C Blue No. 2 Aluminum Lake, FD&C Red No. 40 Aluminum Lake, propylene glycol and shellac glaze.

The structural formula of meclofenamate sodium is:

Molecular Formula: C14H10Cl2NNaO2•H2O

It is a white to creamy white, odorless to almost odorless, crystalline powder with melting point 287° to 291°C, molecular weight 336.15, and it is freely soluble in water.

CLINICAL PHARMACOLOGY

Pharmacodynamics

Meclofenamate sodium is a nonsteroidal agent which has demonstrated anti-inflammatory, analgesic, and antipyretic activity in laboratory animals. The mode of action, like that of other nonsteroidal anti-inflammatory agents, is not known. Therapeutic action does not result from pituitary-adrenal stimulation. In animal studies, meclofenamate sodium was found to inhibit prostaglandin synthesis and to compete for binding at the prostaglandin receptor site. In vitro, meclofenamate sodium was found to be an inhibitor of human leukocyte 5-lipoxygenase activity. These properties may be responsible for the anti-inflammatory action of meclofenamate sodium. There is no evidence that meclofenamate sodium alters the course of the underlying disease.

In several human isotope studies, meclofenamate sodium, at a dosage of 300 mg/day, produced a fecal blood loss of 1 to 2 mL per day, and 2 to 3 mL per day at 400 mg/day. Aspirin, at a dosage of 3.6 g/day, caused a fecal blood loss of 6 mL per day.

In a multiple-dose, 1-week study in normal human volunteers, meclofenamate sodium had little or no effect on collagen-induced platelet aggregation, platelet count, or bleeding time. In comparison, aspirin suppressed collagen-induced platelet aggregation and increased bleeding time. The concomitant administration of antacids (aluminum and magnesium hydroxides) does not interfere with absorption of meclofenamate sodium.

Pharmacokinetics

Meclofenamate sodium is rapidly absorbed in man following single and multiple oral doses with peak plasma concentrations occurring in 0.5 to 2 hours. Based on a comparison to a suspension of meclofenamic acid, meclofenamate sodium is completely bioavailable.

The plasma concentrations of meclofenamic acid decline monoexponentially following oral administration. In a study in ten healthy subjects following a single oral dose the apparent elimination half-life ranged from 0.8 to 5.3 hours. After the administration of meclofenamate sodium for 14 days every 8 hours, the apparent elimination half-life ranged from 0.8 to 2.1 hours with no evidence of accumulation of meclofenamic acid in plasma (see Table).

TABLE SUMMARY OF MECLOFENAMATE SODIUM PHARMACOKINETIC PARAMETERS
Mean (Range) Parameter Values (n = 10)
 | Meclofenamic; Acid 100 mg [Administered every 8 hours for 14 days] | Metabolite I [3-Hydroxymethyl metabolite of meclofenamic acid with 20% activity of meclofenamate sodium in vitro]
Cmax mcg/mL [Peak plasma concentration] | 4.8 (1.8 to 7.2) | 1 (0.5 to 1.5)
tmax hr [Time to peak plasma concentration] | 0.9 (0.5 to 1.5) | 2.4 (0.5 to 4)
Cmin mcg/mL [Trough plasma concentration] | 0.2 (0.5 to 1.5) | 0.4 (0.2 to 1.1)
Cl/F mL/min [Oral clearance] | 206 (126 to 342) | ---
Vd/F liters [Oral distribution volume] | 23.3 (9.1 to 43.2) | ---
t1⁄2 hr [Elimination half-life] | 1.3 (0.8 to 2.1) | 15.3 [Estimated from mean data]
% of Dose in Urine Unconjugated | 0 --- | 0.5 (0 to 1.2)
Total | 2.7 (0 to 4.5) | 21.6 (7.5 to 32.6)

Meclofenamic acid is extensively metabolized to an active metabolite (Metabolite I; 3-hydroxymethyl metabolite of meclofenamic acid) and at least six other less well characterized minor metabolites. Only this Metabolite I has been shown in vitro to inhibit cyclooxygenase activity with approximately one fifth the activity of meclofenamate sodium. Metabolite I (3-hydroxymethyl metabolite of meclofenamic acid) with a mean half-life of approximately 15 hours did accumulate following multiple dosing. After the administration of 100 mg meclofenamate sodium for 14 days every 8 hours, Metabolite I reached a peak plasma concentration of only 1 mcg/mL. By contrast, the peak concentration was 4.8 mcg/mL for the parent compound on both days 1 and 14. Therefore, the accumulation of Metabolite I is probably not clinically significant.

Approximately 70% of the administered dose is excreted by the kidneys with 8% to 35% excreted as predominantly conjugated species of meclofenamic acid and Metabolite I (see Table). Other metabolites, whose excretion rates are unknown, account for the remaining 35% to 62% of the dose excreted in the urine. The remainder of the administered dose (approximately 30%) is eliminated in the feces (apparently through biliary excretion). There is insufficient experience to know if meclofenamate sodium or its metabolites accumulate in patients with compromised renal or hepatic function. Therefore, meclofenamate sodium should be used with caution in these patients (see PRECAUTIONS). Trace amounts of meclofenamate sodium are excreted in human breast milk.

Meclofenamic acid is greater than 99% bound to plasma proteins over a wide drug concentration range.

Unlike most NSAIDs, which when administered with food have a decrease in rate but not in extent of absorption, meclofenamic acid is decreased in both. It has been reported that following the administration of meclofenamate sodium capsules one-half hour after a meal, the average extent of bioavailability decreased by 26%, the average peak concentration (Cmax) decreased 4-fold and the time to Cmax was delayed by 3 hours.

Clinical Studies

Controlled clinical trials comparing meclofenamate sodium with aspirin demonstrated comparable efficacy in rheumatoid arthritis.

The meclofenamate sodium treated patients had fewer reactions involving the special senses, specifically tinnitus, but more gastrointestinal reactions, specifically diarrhea.

The incidence of patients who discontinued therapy due to adverse reactions was similar for both the meclofenamate sodium and aspirin-treated groups.

The improvement with meclofenamate sodium reported by patients and the reduction of the disease activity as evaluated by both physicians and patients with rheumatoid arthritis are associated with a significant reduction in number of tender joints, severity of tenderness, and duration of morning stiffness.

The improvement reported by patients and as evaluated by physicians in patients treated with meclofenamate sodium for osteoarthritis is associated with a significant reduction in night pain, pain on walking, degree of starting pain, and pain on passive motion. The function of knee joints also improved significantly.

Meclofenamate sodium has been used in combination with gold salts or corticosteroids in patients with rheumatoid arthritis. Studies have demonstrated that meclofenamate sodium contributes to the improvement of patients’ conditions while maintained on gold salts or corticosteroids. Data are inadequate to demonstrate that meclofenamate sodium in combination with salicylates produces greater improvement than that achieved with meclofenamate sodium alone.

In controlled clinical trials of patients with mild to moderate pain, meclofenamate sodium 50 mg provided significant pain relief. In these studies of episiotomy and dental pain, meclofenamate sodium 100 mg demonstrated additional benefit in some patients. The onset of analgesic effect was generally within one hour and the duration of action was 4 to 6 hours.

In controlled clinical trials of patients with dysmenorrhea, meclofenamate sodium 100 mg t.i.d. provided significant reduction in the symptoms associated with dysmenorrhea.

In randomized double-blind crossover trials of meclofenamate sodium 100 mg t.i.d. versus placebo in women with heavy menstrual blood loss (MBL), meclofenamate sodium treatment was usually associated with a reduction in menstrual flow.

The graph below is a scatter plot of menstrual flow from the average of two menstrual periods on meclofenamate sodium treatments (vertical axis) versus two menstrual periods on placebo (horizontal axis) for 55 women. Of note, although the amount of reduction in MBL was variable, some degree of reduction occurred in 90% of women in this study.

Scattergram of Menstrual Flow Average of Two Periods on Each Treatment of 55 Women from Three Clinical Trials

The points on the graph represent the mean MBL for each subject when treated for two periods with placebo and two periods with meclofenamate sodium. To ease in interpretation, the following examples may be helpful. Point A represents a woman who had MBL of 459 mL while on placebo, and 405 mL on meclofenamate sodium. Point B represents a woman who had MBL of 472 mL while on placebo, and 64 mL when treated with meclofenamate sodium.

In association with this reduction in menstrual blood loss, the duration of menses was decreased by one day; tampon/pad usage was decreased by an average of two per day on the 2 days of heaviest flow; and symptoms of dysmenorrhea were significantly reduced.

INDICATIONS AND USAGE

Carefully consider the potential benefits and risks of meclofenamate sodium capsules and other treatment options before deciding to use meclofenamate sodium capsules. Use the lowest effective dose for the shortest duration consistent with individual patient treatment goals (see WARNINGS).

Meclofenamate sodium capsules are indicated:

- For reduction of fever in adults
- For relief of mild to moderate pain in adults
- For relief of signs and symptoms of juvenile arthritis.
- For relief of the signs and symptoms of rheumatoid arthritis
- For relief of the signs and symptoms of osteoarthritis.
- For treatment of primary dysmenorrhea.
- For acute or long-term use in the relief of signs and symptoms of the following:
  1. Ankylosing spondylitis
  2. Acute painful shoulder (Acute subacromial bursitis/supraspinatus tendinitis)
  3. Acute gouty arthritis

Meclofenamate sodium capsules are also indicated for the treatment of idiopathic heavy menstrual blood loss (see CLINICAL PHARMACOLOGY and PRECAUTIONS).

As with all nonsteroidal anti-inflammatory drugs, selection of meclofenamate sodium capsules require a careful assessment of the benefit/risk ratio (see WARNINGS, PRECAUTIONS and ADVERSE REACTIONS).

Meclofenamate sodium capsules are not recommended in children because adequate studies to demonstrate safety and efficacy have not been carried out.

CONTRAINDICATIONS

Meclofenamate sodium capsules are contraindicated in patients with known hypersensitivity to meclofenamate sodium.

Meclofenamate sodium capsules should not be given to patients who have experienced asthma, urticaria, or allergic-type reactions after taking aspirin or other NSAIDs. Severe, rarely fatal, anaphylactic-like reactions to NSAIDs have been reported in such patients (see WARNINGS: Anaphylactoid Reactions and PRECAUTIONS: Preexisting Asthma).

Meclofenamate sodium capsules are contraindicated in the setting of coronary artery bypass graft (CABG) surgery (see WARNINGS).

WARNINGS

Cardiovascular Effects

Cardiovascular Thrombotic Events

Clinical trials of several COX-2 selective and nonselective NSAIDs of up to 3 years duration have shown an increased risk of serious cardiovascular (CV) thrombotic events, including myocardial infarction (MI) and stroke, which can be fatal. Based on available data, it is unclear that the risk for CV thrombotic events is similar for all NSAIDs. The relative increase in serious CV thrombotic events over baseline conferred by NSAID use appears to be similar in those with and without known CV disease or risk factors for CV disease. However, patients with known CV disease or risk factors had a higher absolute incidence of excess serious CV thrombotic events, due to their increased baseline rate. Some observational studies found that this increased risk of serious CV thrombotic events began as early as the first weeks of treatment. The increase in CV thrombotic risk has been observed most consistently at higher doses.

To minimize the potential risk for an adverse CV event in NSAID-treated patients, use the lowest effective dose for the shortest duration possible. Physicians and patients should remain alert for the development of such events, throughout the entire treatment course, even in the absence of previous CV symptoms. Patients should be informed about the symptoms of serious CV events and the steps to take if they occur.

There is no consistent evidence that concurrent use of aspirin mitigates the increased risk of serious CV thrombotic events associated with NSAID use. The concurrent use of aspirin and an NSAID, such as meclofenamate sodium, increases the risk of serious gastrointestinal (GI) events (see WARNINGS).

Status Post Coronary Artery Bypass Graft (CABG) Surgery

Two large, controlled clinical trials of a COX-2 selective NSAID for the treatment of pain in the first 10 to 14 days following CABG surgery found an increased incidence of myocardial infarction and stroke. NSAIDs are contraindicated in the setting of CABG (see CONTRAINDICATIONS).

Post-MI Patients

Observational studies conducted in the Danish National Registry have demonstrated that patients treated with NSAIDs in the post-MI period were at increased risk of reinfarction, CV-related death, and all-cause mortality beginning in the first week of treatment. In this same cohort, the incidence of death in the first year post MI was 20 per 100 person years in NSAID-treated patients compared to 12 per 100 person years in non-NSAID exposed patients. Although the absolute rate of death declined somewhat after the first year post-MI, the increased relative risk of death in NSAID users persisted over at least the next 4 years of follow-up.

Avoid the use of meclofenamate sodium capsules in patients with a recent MI unless the benefits are expected to outweigh the risk of recurrent CV thrombotic events. If meclofenamate sodium capsules are used in patients with a recent MI, monitor patients for signs of cardiac ischemia.

Hypertension

NSAIDs, including meclofenamate sodium, can lead to onset of new hypertension or worsening of preexisting hypertension, either of which may contribute to the increased incidence of CV events. Patients taking thiazides or loop diuretics may have impaired response to these therapies when taking NSAIDs. NSAIDs, including meclofenamate sodium, should be used with caution in patients with hypertension. Blood pressure (BP) should be monitored closely during the initiation of NSAID treatment and throughout the course of therapy.

Heart Failure and Edema

The Coxib and traditional NSAID Trialists’ Collaboration meta-analysis of randomized controlled trials demonstrated an approximately 2-fold increase in hospitalizations for heart failure in COX-2 selective-treated patients and nonselective NSAID-treated patients compared to placebo-treated patients. In a Danish National Registry study of patients with heart failure, NSAID use increased the risk of MI, hospitalization for heart failure, and death.

Additionally, fluid retention and edema have been observed in some patients treated with NSAIDs. Use of meclofenamate sodium may blunt the CV effects of several therapeutic agents used to treat these medical conditions [e.g., diuretics, ACE inhibitors, or angiotensin receptor blockers (ARBs)] (see Drug Interactions).

Avoid the use of meclofenamate sodium capsules in patients with severe heart failure unless the benefits are expected to outweigh the risk of worsening heart failure. If meclofenamate sodium capsules are used in patients with severe heart failure, monitor patients for signs of worsening heart failure.

Gastrointestinal Effects

Risk of Ulceration, Bleeding, and Perforation

NSAIDs, including meclofenamate sodium, can cause serious gastrointestinal (GI) adverse events including inflammation, bleeding, ulceration, and perforation of the stomach, small intestine, or large intestine, which can be fatal. These serious adverse events can occur at any time, with or without warning symptoms, in patients treated with NSAIDs. Only one in five patients, who develop a serious upper GI adverse event on NSAID therapy, is symptomatic. Upper GI ulcers, gross bleeding, or perforation caused by NSAIDs occur in approximately 1% of patients treated for 3 to 6 months, and in about 2% to 4% of patients treated for one year. These trends continue with longer duration of use, increasing the likelihood of developing a serious GI event at some time during the course of therapy. However, even short-term therapy is not without risk.

NSAIDs should be prescribed with extreme caution in those with a prior history of ulcer disease or gastrointestinal bleeding. Patients with a prior history of peptic ulcer disease and/or gastrointestinal bleeding who use NSAIDs have a greater than 10-fold increased risk for developing a GI bleed compared to patients with neither of these risk factors. Other factors that increase the risk for GI bleeding in patients treated with NSAIDs include concomitant use of oral corticosteroids or anticoagulants, longer duration of NSAID therapy, smoking, use of alcohol, older age, and poor general health status. Most spontaneous reports of fatal GI events are in elderly or debilitated patients and therefore, special care should be taken in treating this population.

To minimize the potential risk for an adverse GI event in patients treated with an NSAID, the lowest effective dose should be used for the shortest possible duration. Patients and physicians should remain alert for signs and symptoms of GI ulceration and bleeding during NSAID therapy and promptly initiate additional evaluation and treatment if a serious GI adverse event is suspected. This should include discontinuation of the NSAID until a serious GI adverse event is ruled out. For high risk patients, alternate therapies that do not involve NSAIDs should be considered.

Renal Effects

Long-term administration of NSAIDs has resulted in renal papillary necrosis and other renal injury. Renal toxicity has also been seen in patients in whom renal prostaglandins have a compensatory role in the maintenance of renal perfusion. In these patients, administration of a nonsteroidal anti-inflammatory drug may cause a dose dependent reduction in prostaglandin formation and, secondarily, in renal blood flow, which may precipitate overt renal decompensation. Patients at greatest risk of this reaction are those with impaired renal function, heart failure, liver dysfunction, those taking diuretics and ACE inhibitors, and the elderly. Discontinuation of NSAID therapy is usually followed by recovery to the pretreatment state.

Advanced Renal Disease

No information is available from controlled clinical studies regarding the use of meclofenamate sodium in patients with advanced renal disease. Therefore, treatment with meclofenamate sodium is not recommended in these patients with advanced renal disease. If meclofenamate sodium therapy must be initiated, close monitoring of the patient's renal function is advisable.

Anaphylactoid Reactions

As with other NSAIDs, anaphylactoid reactions may occur in patients without known prior exposure to meclofenamate sodium. Meclofenamate sodium should not be given to patients with the aspirin triad. This symptom complex typically occurs in asthmatic patients who experience rhinitis with or without nasal polyps, or who exhibit severe, potentially fatal bronchospasm after taking aspirin or other NSAIDs (see CONTRAINDICATIONS and PRECAUTIONS: Preexisting Asthma). Emergency help should be sought in cases where an anaphylactoid reaction occurs.

Serious Skin Reactions

NSAIDs, including meclofenamate sodium, can cause serious skin adverse reactions such as exfoliative dermatitis, Stevens-Johnson Syndrome (SJS), and toxic epidermal necrolysis (TEN), which can be fatal. NSAIDs can also cause fixed drug eruption (FDE). FDE may present as a more severe variant knows as generalized bullous fixed drug eruption (GBFDE), which can be life-threatening. These serious events may occur without warning. Inform patients about the signs and symptoms of serious skin reactions, and to discontinue the use of meclofenamate sodium capsules at the first appearance of skin rash or any other sign of hypersensitivity. Meclofenamate sodium capsules are contraindicated in patients with previous serious skin reactions to NSAIDs (see CONTRAINDICATIONS).

Drug Reaction with Eosinophilia and Systemic Symptoms (DRESS) has been reported in patients taking NSAIDs such as meclofenamate sodium capsules. Some of these events have been fatal or life-threatening. DRESS typically, although not exclusively, presents with fever, rash, lymphadenopathy, and/or facial swelling. Other clinical manifestations may include hepatitis, nephritis, hematological abnormalities, myocarditis, or myositis. Sometimes symptoms of DRESS may resemble an acute viral infection. Eosinophilia is often present. Because this disorder is variable in its presentation, other organ systems not noted here may be involved. It is important to note that early manifestations of hypersensitivity, such as fever or lymphadenopathy, may be present even though rash is not evident. If such signs or symptoms are present, discontinue meclofenamate sodium capsules and evaluate the patient immediately.

Fetal Toxicity

Premature Closure of Fetal Ductus Arteriosus

Avoid use of NSAIDs, including meclofenamate sodium capsules, in pregnant women at about 30 weeks gestation and later. NSAIDs including meclofenamate sodium capsules, increase the risk of premature closure of the fetal ductus arteriosus at approximately this gestational age.

Oligohydramnios/Neonatal Renal Impairment

Use of NSAIDs, including meclofenamate sodium capsules, at about 20 weeks gestation or later in pregnancy may cause fetal renal dysfunction leading to oligohydramnios and, in some cases, neonatal renal impairment. These adverse outcomes are seen, on average, after days to weeks of treatment, although oligohydramnios has been infrequently reported as soon as 48 hours after NSAID initiation. Oligohydramnios is often, but not always, reversible with treatment discontinuation. Complications of prolonged oligohydramnios may, for example, include limb contractures and delayed lung maturation. In some postmarketing cases of impaired neonatal renal function, invasive procedures such as exchange transfusion or dialysis were required.

If NSAID treatment is necessary between about 20 weeks and 30 weeks gestation, limit meclofenamate sodium capsules use to the lowest effective dose and shortest duration possible. Consider ultrasound monitoring of amniotic fluid if meclofenamate sodium capsules treatment extends beyond 48 hours. Discontinue meclofenamate sodium capsules if oligohydramnios occurs and follow up according to clinical practice (see PRECAUTIONS: Pregnancy).

PRECAUTIONS

General

Meclofenamate sodium cannot be expected to substitute for corticosteroids or to treat corticosteroid insufficiency. Abrupt discontinuation of corticosteroids may lead to disease exacerbation. Patients on prolonged corticosteroid therapy should have their therapy tapered slowly if a decision is made to discontinue corticosteroids.

The pharmacological activity of meclofenamate sodium in reducing fever and inflammation may diminish the utility of these diagnostic signs in detecting complications of presumed noninfectious, painful conditions.

Hepatic Effects

Borderline elevations of one or more liver tests may occur in up to 15% of patients taking NSAIDs including meclofenamate sodium. These laboratory abnormalities may progress, may remain unchanged, or may be transient with continuing therapy. Notable elevations of ALT or AST (approximately 3 or more times the upper limit of normal) have been reported in approximately 1% of patients in clinical trials with NSAIDs. In addition, rare cases of severe hepatic reactions, including jaundice and fatal fulminant hepatitis, liver necrosis and hepatic failure, some of them with fatal outcomes have been reported.

A patient with symptoms and/or signs suggesting liver dysfunction, or in whom an abnormal liver test has occurred, should be evaluated for evidence of the development of a more severe hepatic reaction while on therapy with meclofenamate sodium. If clinical signs and symptoms consistent with liver disease develop, or if systemic manifestations occur (e.g., eosinophilia, rash, etc.), meclofenamate sodium should be discontinued.

Hematological Effects

Anemia is sometimes seen in patients receiving NSAIDs, including meclofenamate sodium. This may be due to fluid retention, occult or gross GI blood loss, or an incompletely described effect upon erythropoiesis. Patients on long-term treatment with NSAIDs, including meclofenamate sodium, should have their hemoglobin or hematocrit checked if they exhibit any signs or symptoms of anemia.

NSAIDs inhibit platelet aggregation and have been shown to prolong bleeding time in some patients. Unlike aspirin, their effect on platelet function is quantitatively less, of shorter duration, and reversible. Patients receiving meclofenamate sodium who may be adversely affected by alterations in platelet function, such as those with coagulation disorders or patients receiving anticoagulants, should be carefully monitored.

Preexisting Asthma

Patients with asthma may have aspirin-sensitive asthma. The use of aspirin in patients with aspirin-sensitive asthma has been associated with severe bronchospasm which can be fatal. Since cross reactivity, including bronchospasm, between aspirin and other nonsteroidal anti-inflammatory drugs has been reported in such aspirin-sensitive patients, meclofenamate sodium should not be administered to patients with this form of aspirin sensitivity and should be used with caution in patients with preexisting asthma.

Information for Patients

Patients should be informed of the following information before initiating therapy with an NSAID and periodically during the course of ongoing therapy. Patients should also be encouraged to read the NSAID Medication Guide that accompanies each prescription dispensed.

1. Cardiovascular Thrombotic Events: Advise patients to be alert for the symptoms of cardiovascular thrombotic events, including chest pain, shortness of breath, weakness, or slurring of speech, and to report any of these symptoms to their healthcare provider immediately (see WARNINGS).
2. Meclofenamate sodium, like other NSAIDs, can cause GI discomfort and, rarely, serious GI side effects, such as ulcers and bleeding, which may result in hospitalization and even death. Although serious GI tract ulcerations and bleeding can occur without warning symptoms, patients should be alert for the signs and symptoms of ulcerations and bleeding, and should ask for medical advice when observing any indicative sign or symptoms including epigastric pain, dyspepsia, melena, and hematemesis. Patients should be apprised of the importance of this follow-up (see WARNINGS: Gastrointestinal Effects: Risk of Ulceration, Bleeding, and Perforation).
3. Serious Skin Reactions, including DRESS: Advise patients to stop taking meclofenamate sodium capsules immediately if they develop any type of rash or fever and to contact their healthcare provider as soon as possible (see WARNINGS).
4. Heart Failure and Edema: Advise patients to be alert for the symptoms of congestive heart failure including shortness of breath, unexplained weight gain, or edema and to contact their healthcare provider if such symptoms occur (see WARNINGS).
5. Patients should be informed of the warning signs and symptoms of hepatotoxicity (e.g., nausea, fatigue, lethargy, pruritus, jaundice, right upper quadrant tenderness, and “flu-like” symptoms). If these occur, patients should be instructed to stop therapy and seek immediate medical therapy.
6. Patients should be informed of the signs of an anaphylactoid reaction (e.g., difficulty breathing, swelling of the face or throat). If these occur, patients should be instructed to seek immediate emergency help (see WARNINGS).
7. Fetal Toxicity: Inform pregnant women to avoid use of meclofenamate sodium capsules and other NSAIDs starting at 30 weeks gestation because of the risk of the premature closing of the fetal ductus arteriosus. If treatment with meclofenamate sodium capsules is needed for a pregnant woman between about 20 to 30 weeks gestation, advise her that she may need to be monitored for oligohydramnios, if treatment continues for longer than 48 hours (see WARNINGS: Fetal Toxicity, PRECAUTIONS: Pregnancy).

Laboratory Tests

Because serious GI tract ulcerations and bleeding can occur without warning symptoms, physicians should monitor for signs or symptoms of GI bleeding. Patients on long-term treatment with NSAIDs, should have their CBC and a chemistry profile checked periodically. If clinical signs and symptoms consistent with liver or renal disease develop, systemic manifestations occur (e.g., eosinophilia, rash, etc.) or if abnormal liver tests persist or worsen, meclofenamate sodium should be discontinued.

Drug Interactions

ACE-inhibitors

Reports suggest that NSAIDs may diminish the antihypertensive effect of ACE-inhibitors. This interaction should be given consideration in patients taking NSAIDs concomitantly with ACE-inhibitors.

Aspirin

When meclofenamate sodium in administered with aspirin, its protein binding is reduced, although the clearance of free meclofenamate sodium is not altered. The clinical significance of this interaction is not known; however, as with other NSAIDs, concomitant administration of meclofenamate sodium capsules and aspirin is not generally recommended because of the potential of increased adverse effects.

Furosemide

Clinical studies, as well as post-marketing observations, have shown that meclofenamate sodium can reduce the natriuretic effect-of furosemide and thiazides in some patients. This response has been attributed to inhibition of renal prostaglandin synthesis. During concomitant therapy with NSAIDs, the patient should be observed closely for signs of renal failure (see PRECAUTIONS: Renal Effects), as well as to assure diuretic efficacy.

Lithium

NSAIDs have produced an elevation of plasma lithium levels and a reduction in renal lithium clearance. The mean minimum lithium concentration increased 15% and the renal clearance was decreased by approximately 20%. These effects have been attributed to inhibition of renal prostaglandin synthesis by the NSAID. Thus, when NSAIDs and lithium are administered concurrently, subjects should be observed carefully for signs of lithium toxicity.

Methotrexate

NSAIDs have been reported to competitively inhibit methotrexate accumulation in rabbit kidney slices. This may indicate that they could enhance the toxicity of methotrexate. Caution should be used when NSAIDs are administered concomitantly with methotrexate.

Warfarin

The effects of warfarin and NSAIDs on GI bleeding are synergistic, such that users of both drugs together have a risk of serious GI bleeding higher than users of either drug alone.

Carcinogenesis

An 18-month study in rats revealed no evidence of carcinogenicity.

Pregnancy

Risk Summary

Use of NSAIDs, including meclofenamate sodium capsules, can cause premature closure of the fetal ductus arteriosus and fetal renal dysfunction leading to oligohydramnios and, in some cases, neonatal renal impairment. Because of these risks, limit dose and duration of meclofenamate sodium capsules use between about 20 and 30 weeks of gestation, and avoid meclofenamate sodium capsules use at about 30 weeks of gestation and later in pregnancy (see WARNINGS: Fetal Toxicity).

Premature Closure of Fetal Ductus Arteriosus

Use of NSAIDs, including meclofenamate sodium capsules, at about 30 weeks gestation or later in pregnancy increases the risk of premature closure of the fetal ductus arteriosus.

Oligohydramnios/Neonatal Renal Impairment

Use of NSAIDs at about 20 weeks gestation or later in pregnancy has been associated with cases of fetal renal dysfunction leading to oligohydramnios, and in some cases, neonatal renal impairment.

Data from observational studies regarding other potential embryofetal risks of NSAID use in women in the first or second trimesters of pregnancy are inconclusive. Animal reproductive studies conducted in rats and rabbits have not demonstrated evidence of developmental abnormalities. However, animal reproduction studies are not always predictive of human response. Based on animal data, prostaglandins have been shown to have an important role in endometrial vascular permeability, blastocyst implantation, and decidualization. In animal studies, administration of prostaglandin synthesis inhibitors such as meclofenamate, resulted in increased pre- and post-implantation loss. Prostaglandins also have been shown to have an important role in fetal kidney development. In published animal studies, prostaglandin synthesis inhibitors have been reported to impair kidney development when administered at clinically relevant doses. The estimated background risk of major birth defects and miscarriage for the indicated population(s) is unknown. All pregnancies have a background risk of birth defect, loss, or other adverse outcomes. In the U.S. general population, the estimated background risk of major birth defects and miscarriage in clinically recognized pregnancies is 2-4% and 15-20%, respectively.

Clinical Considerations

Fetal/Neonatal Adverse Reactions

Premature Closure of Fetal Ductus Arteriosus

Avoid use of NSAIDs in women at about 30 weeks gestation and later in pregnancy, because NSAIDs, including meclofenamate sodium capsules, can cause premature closure of the fetal ductus arteriosus (see WARNINGS: Fetal Toxicity).

Oligohydramnios/Neonatal Renal Impairment

If an NSAID is necessary at about 20 weeks gestation or later in pregnancy, limit the use to the lowest effective dose and shortest duration possible. If meclofenamate sodium capsules treatment extends beyond 48 hours, consider monitoring with ultrasound for oligohydramnios. If oligohydramnios occurs, discontinue meclofenamate sodium capsules and follow up according to clinical practice (see WARNINGS: Fetal Toxicity).

Data

Human Data

Premature Closure of Fetal Ductus Arteriosus

Published literature reports that the use of NSAIDs at about 30 weeks of gestation and later in pregnancy may cause premature closure of the fetal ductus arteriosus.

Oligohydramnios/Neonatal Renal Impairment

Published studies and postmarketing reports describe maternal NSAID use at about 20 weeks gestation or later in pregnancy associated with fetal renal dysfunction leading to oligohydramnios, and in some cases, neonatal renal impairment. These adverse outcomes are seen, on average, after days to weeks of treatment, although oligohydramnios has been infrequently reported as soon as 48 hours after NSAID initiation. In many cases, but not all, the decrease in amniotic fluid was transient and reversible with cessation of the drug. There have been a limited number of case reports of maternal NSAID use and neonatal renal dysfunction without oligohydramnios, some of which were irreversible. Some cases of neonatal renal dysfunction required treatment with invasive procedures, such as exchange transfusion or dialysis.

Methodological limitations of these postmarketing studies and reports include lack of a control group; limited information regarding dose, duration, and timing of drug exposure; and concomitant use of other medications. These limitations preclude establishing a reliable estimate of the risk of adverse fetal and neonatal outcomes with maternal NSAID use. Because the published safety data on neonatal outcomes involved mostly preterm infants, the generalizability of certain reported risks to the full-term infant exposed to NSAIDs through maternal use is uncertain.

Labor and Delivery

In rat studies with NSAIDs, as with other drugs known to inhibit prostaglandin synthesis, an increased incidence of dystocia, delayed parturition, and decreased pup survival occurred. The effects of meclofenamate sodium on labor and delivery in pregnant women are unknown.

Nursing Mothers

It is not known whether this drug is excreted in human milk. Because many drugs are excreted in human-milk and because of the potential for serious adverse reactions in nursing infants from meclofenamate sodium, a decision should be made whether to discontinue nursing or to discontinue the drug, taking into account the importance of the drug to the mother.

Pediatric Use

Safety and effectiveness in pediatric patients below the age of 14 have not been established.

Geriatric Use

As with any NSAIDs, caution should be exercised in treating the elderly (65 years and older).

ADVERSE REACTIONS

Incidence Greater Than 1%

The following adverse reactions were observed in clinical trials and included observations from more than 2,700 patients, 594 of whom were treated for one year and 248 for at least 2 years.

Gastrointestinal

The most frequently reported adverse reactions associated with meclofenamate sodium involve the gastrointestinal system. In controlled studies of up to 6 months duration, these disturbances occurred in the following decreasing order of frequency with the approximate incidences in parentheses: diarrhea (10% to 33%), nausea with or without vomiting (11%), other gastrointestinal disorders (10%), and abdominal pain*. In long-term uncontrolled studies of up to 4 years duration, one third of the patients had at least one episode of diarrhea some time during meclofenamate sodium therapy.

In approximately 4% of the patients in controlled studies, diarrhea was severe enough to require discontinuation of meclofenamate sodium. The occurrence of diarrhea is dose related, generally subsides with dose reduction, and clears with termination of therapy. The incidence of diarrhea in patients with osteoarthritis is generally lower than that reported in patients with rheumatoid arthritis.

Other reactions less frequently reported were pyrosis*, flatulence*, anorexia, constipation, stomatitis, and peptic ulcer. The majority of the patients with peptic ulcer had either a history of ulcer disease or were receiving concomitant anti-inflammatory drugs, including corticosteroids which are known to produce peptic ulceration.

Cardiovascular: edema

Dermatologic: rash*, urticaria, pruritus

Central Nervous System: headache*, dizziness*

Special Senses: tinnitus

* Incidence between 3% and 9%. Those reactions occurring in 1% to 3% of patients are not marked with an asterisk.

Incidence Less Than 1%—Probably Causally Related

The following adverse reactions were reported less frequently than 1% during controlled clinical trials and through voluntary reports since marketing. The probability of a causal relationship exists between the drug and these adverse reactions.

Gastrointestinal: bleeding and/or perforation with or without obvious ulcer formation, colitis, cholestatic jaundice

Renal: renal failure

Hematologic: neutropenia, thrombocytopenic purpura, leukopenia, agranulocytosis, hemolytic anemia, eosinophilia, decrease in hemoglobin and/or hematocrit

Dermatologic: erythema multiforme, Stevens-Johnson Syndrome, exfoliative dermatitis, toxic epidermal necrolysis (TEN), and fixed drug eruption (FDE)

Hepatic: alteration of liver function tests

Allergic: lupus and serum sickness-like symptoms

Incidence Less Than 1%—Causal Relationship Unknown

Other reactions have been reported but under conditions where a causal relationship could not be established. However, in these rarely reported events, that possibility cannot be excluded. Therefore, these observations are listed to alert physicians.

Cardiovascular: palpitations

Central Nervous System: malaise, fatigue, paresthesia, insomnia, depression

Special Senses: blurred vision, taste disturbances, decreased visual acuity, temporary loss of vision, reversible loss of color vision, retinal changes including macular fibrosis, macular and perimacular edema, conjunctivitis, iritis

Renal: nocturia

Gastrointestinal: paralytic ileus

Dermatologic: erythema nodosum, hair loss

OVERDOSAGE

The following is based on the little information available concerning overdosage with meclofenamate sodium and related compounds. After a massive overdose, CNS stimulation may be manifested by irrational behavior, marked agitation and generalized seizures. Following this phase, renal toxicity (falling urine output, rising creatinine, abnormal urinary cellular elements) may be noted with possible oliguria or anuria and azotemia. A 24 year-old male was anuric for approximately one week after ingesting an overdose of 6 to 7 grams of meclofenamate sodium. Spontaneous diuresis and recovery subsequently occurred.

Management consists of emptying the stomach by emesis or lavage and instilling an ample dose of activated charcoal into the stomach. There is some evidence that charcoal will actively absorb meclofenamate sodium, but dialysis or hemoperfusion may be less effective because of plasma protein binding. The seizures should be controlled by an appropriate anticonvulsant regimen. Attention should be directed throughout, by careful monitoring, to the preservation of vital functions and fluid-electrolyte balance. Dialysis may be required to correct serious azotemia or electrolyte imbalance.

DOSAGE AND ADMINISTRATION

Carefully consider the potential benefits and risks of meclofenamate sodium capsules and other treatment options before deciding to use meclofenamate sodium capsules. Use the lowest effective dose for the shortest duration consistent with individual patient treatment goals (see WARNINGS).

After observing the response to initial therapy with meclofenamate sodium capsules, the dose and frequency should be adjusted to suit an individual patient's needs.

Usual Dosage

For Mild to Moderate Pain

The recommended dose is 50 mg every 4 to 6 hours. Doses of 100 mg may be needed in some patients for optimal pain relief (see CLINICAL PHARMACOLOGY). However, the daily dose should not exceed 400 mg (see ADVERSE REACTIONS).

For excessive menstrual blood loss and primary dysmenorrheal

The recommended dose of meclofenamate sodium is 100 mg 3 times a day, for up to 6 days, starting at the onset of menstrual flow.

For rheumatoid arthritis and osteoarthritis (including acute exacerbations of chronic disease)

The dosage is 200 mg to 400 mg per day, administered in three or four equal doses.

Therapy should be initiated at the lower dosage, then increased as necessary to improve clinical response. The dosage should be individually adjusted for each patient, depending on the severity of the symptoms and the clinical response. The daily dosage should not exceed 400 mg per day. The smallest dosage of meclofenamate sodium that yields clinical control should be employed.

Although improvement may be seen in some patients in a few days, 2 to 3 weeks of treatment may be required to obtain the optimum therapeutic benefit.

After a satisfactory response has been achieved, the dosage should be adjusted as required. A lower dosage may suffice for long-term administration.

If gastrointestinal complaints occur (see WARNINGS and PRECAUTIONS), meclofenamate sodium may be administered with meals or with milk (see CLINICAL PHARMACOLOGY for a description of food effects). If intolerance occurs, the dosage may need to be reduced. Therapy should be terminated if any severe adverse reactions occur.

HOW SUPPLIED

Meclofenamate Sodium Capsules, USP are available containing either 50 mg or 100 mg of meclofenamic acid as the sodium salt.

The 50 mg capsules are hard-shell gelatin capsules with a coral opaque cap and a coral opaque body filled with an off-white powder blend. The capsules are axially printed with MYLAN over 2150 in black ink on both the cap and body. They are available as follows:

NDC 0378-2150-01
bottles of 100 capsules

The 100 mg capsules are hard-shell gelatin capsules with a coral opaque cap and a white opaque body filled with an off-white powder blend. The capsules are axially printed with MYLAN over 3000 in black ink on both the cap and body. They are available as follows:

NDC 0378-3000-01
bottles of 100 capsules

Store at 20° to 25°C (68° to 77°F). [See USP Controlled Room Temperature.]

Protect from light and moisture.

Dispense in a tight, light-resistant container as defined in the USP using a child-resistant closure.

PHARMACIST: Dispense a Medication Guide with each prescription.

Medication Guide for Nonsteroidal Anti-inflammatory Drugs (NSAIDs)

What is the most important information I should know about medicines called Nonsteroidal Anti-inflammatory Drugs (NSAIDs)?

NSAIDs can cause serious side effects, including:

- Increased risk of a heart attack or stroke that can lead to death. This risk may happen early in treatment and may increase:
  - with increasing doses of NSAIDs
  - with longer use of NSAIDs
Do not take NSAIDs right before or after a heart surgery called a “coronary artery bypass graft (CABG)."
Avoid taking NSAIDs after a recent heart attack, unless your healthcare provider tells you to. You may have an increased risk of another heart attack if you take NSAIDs after a recent heart attack.
- Increased risk of bleeding, ulcers, and tears (perforation) of the esophagus (tube leading from the mouth to the stomach), stomach and intestines:
  - anytime during use
  - without warning symptoms
  - that may cause death
The risk of getting an ulcer or bleeding increases with:
  1. past history of stomach ulcers, or stomach or intestinal bleeding with use of NSAIDs
  2. taking medicines called “corticosteroids”, “anticoagulants”, “SSRIs”, or “SNRIs”

- increasing doses of NSAIDs
- longer use of NSAIDs
- smoking
- drinking alcohol

- older age
- poor health
- advanced liver disease
- bleeding problems

NSAIDs should only be used:

- exactly as prescribed
- at the lowest dose possible for your treatment
- for the shortest time needed

What are NSAIDs?

NSAIDs are used to treat pain and redness, swelling, and heat (inflammation) from medical conditions such as different types of arthritis, menstrual cramps, and other types of short-term pain.

Who should not take NSAIDs?

Do not take NSAIDs:

- if you have had an asthma attack, hives, or other allergic reaction with aspirin or any other NSAIDs.
- right before or after heart bypass surgery.

Before taking NSAIDs, tell your healthcare provider about all of your medical conditions, including if you:

- have liver or kidney problems
- have high blood pressure
- have asthma
- are pregnant or plan to become pregnant. Taking NSAIDs at about 20 weeks of pregnancy or later may harm your unborn baby. If you need to take NSAIDs for more than 2 days when you are between 20 and 30 weeks of pregnancy, your healthcare provider may need to monitor the amount of fluid in your womb around your baby. You should not take NSAIDs after about 30 weeks of pregnancy.
- are breastfeeding or plan to breast feed.

Tell your healthcare provider about all of the medicines you take, including prescription or over-the-counter medicines, vitamins or herbal supplements. NSAIDs and some other medicines can interact with each other and cause serious side effects. Do not start taking any new medicine without talking to your healthcare provider first.

What are the possible side effects of NSAIDs?

NSAIDs can cause serious side effects, including:

See “What is the most important information I should know about medicines called Nonsteroidal Anti-inflammatory Drugs (NSAIDs)?”

- new or worse high blood pressure
- heart failure
- liver problems including liver failure
- kidney problems including kidney failure
- low red blood cells (anemia)
- life-threatening skin reactions
- life threatening allergic reactions
- Other side effects of NSAIDs include: stomach pain, constipation, diarrhea, gas, heartburn, nausea, vomiting, and dizziness.

Get emergency help right away if you get any of the following symptoms:

- shortness of breath or trouble breathing
- chest pain
- weakness in one part or side of your body

- slurred speech
- swelling of the face or throat

Stop taking your NSAID and call your healthcare provider right away if you get any of the following symptoms:

- nausea
- more tired or weaker than usual
- diarrhea
- itching
- your skin or eyes look yellow
- indigestion or stomach pain
- flu-like symptoms

- vomit blood
- there is blood in your bowel movement or it is black and sticky like tar
- unusual weight gain
- skin rash or blisters with fever
- swelling of the arms, legs, hands and feet

If you take too much of your NSAID, call your healthcare provider or get medical help right away.

These are not all the possible side effects of NSAIDs. For more information, ask your healthcare provider or pharmacist about NSAIDs.

Call your doctor for medical advice about side effects. You may report side effects to FDA at 1-800-FDA-1088.

Other information about NSAIDs

- Aspirin is an NSAID but it does not increase the chance of a heart attack. Aspirin can cause bleeding in the brain, stomach, and intestines. Aspirin can also cause ulcers in the stomach and intestines.
- Some NSAIDs are sold in lower doses without a prescription (over-the-counter). Talk to your healthcare provider before using over-the-counter NSAIDs for more than 10 days.

General information about the safe and effective use of NSAIDs

Medicines are sometimes prescribed for purposes other than those listed in a Medication Guide. Do not use NSAIDs for a condition for which they were not prescribed. Do not give NSAIDs to other people, even if they have the same symptoms that you have. They may harm them.

If you would like more information about NSAIDs, talk with your healthcare provider. You can ask your pharmacist or healthcare provider for information about NSAIDs that is written for health professionals.

Manufactured for: Mylan Pharmaceuticals Inc., Morgantown, WV 26505 U.S.A.

For more information, call Mylan at 1-877-446-3679 (1-877-4-INFO-RX).

This Medication Guide has been approved by the U.S. Food and Drug Administration.

Manufactured for:
Mylan Pharmaceuticals Inc.
Morgantown, WV 26505 U.S.A.

Manufactured by:
Mylan Laboratories Limited
Hyderabad — 500 096, India

75107848

Revised: 12/2024
MX:MCFT:R4m/MX:MG:MCFT:R3m

PRINCIPAL DISPLAY PANEL – 50 mg

NDC 0378-2150-01

Meclofenamate
Sodium
Capsules, USP
50 mg

PHARMACIST: Dispense the accompanying
Medication Guide to each patient.

Rx only 100 Capsules

Each capsule contains:
Meclofenamate sodium, USP monohydrate
equivalent to 50 mg of meclofenamate acid.

Usual Dosage: 200 mg to 400 mg per day;
administered in three or four equal doses.

See package outsert for full prescribing
information.

Keep this and all medication out of
the reach of children.

Store at 20° to 25°C (68° to 77°F). [See
USP Controlled Room Temperature.]

Protect from light and moisture.

Manufactured for:
Mylan Pharmaceuticals Inc.
Morgantown, WV 26505 U.S.A.

Made in India

Mylan.com

RMX2150A1

Dispense in a tight, light-resistant
container as defined in the USP
using a child-resistant closure.

Keep container tightly closed.

Code No.: MH/DRUGS/25/NKD/89

PRINCIPAL DISPLAY PANEL – 100 mg

NDC 0378-3000-01

Meclofenamate
Sodium
Capsules, USP
100 mg

PHARMACIST: Dispense the accompanying
Medication Guide to each patient.

Rx only 100 Capsules

Each capsule contains:
Meclofenamate sodium, USP monohydrate
equivalent to 100 mg of meclofenamate acid.

Usual Dosage: 200 mg to 400 mg per day;
administered in three or four equal doses.

See package outsert for full prescribing
information.

Keep this and all medication out of
the reach of children.

Store at 20° to 25°C (68° to 77°F). [See
USP Controlled Room Temperature.]

Protect from light and moisture.

Manufactured for:
Mylan Pharmaceuticals Inc.
Morgantown, WV 26505 U.S.A.

Made in India

Mylan.com

RMX3000A1

Dispense in a tight, light-resistant
container as defined in the USP
using a child-resistant closure.

Keep container tightly closed.

Code No.: MH/DRUGS/25/NKD/89